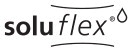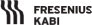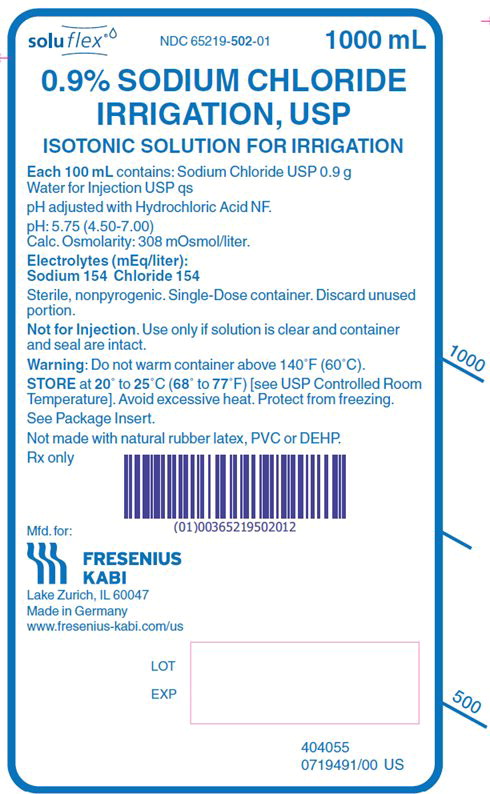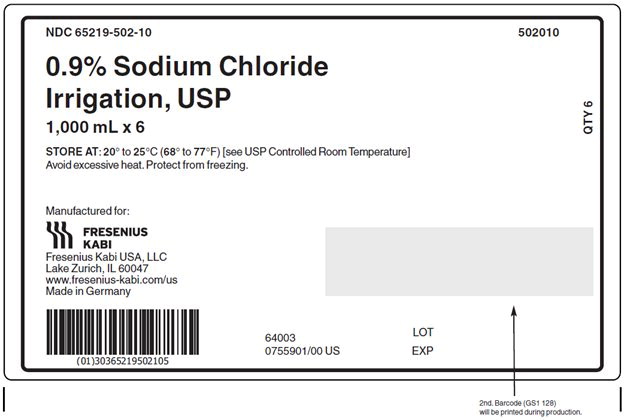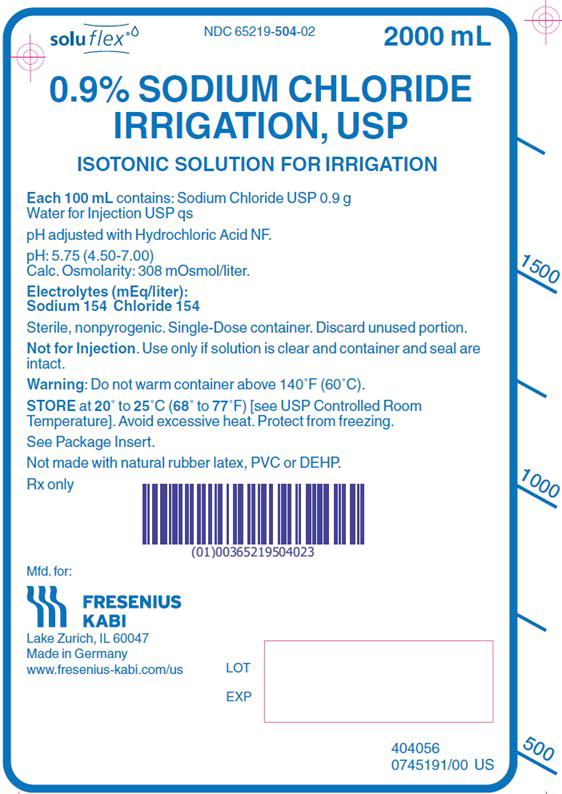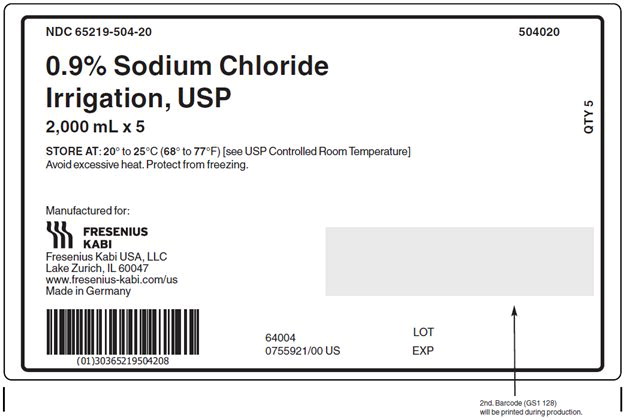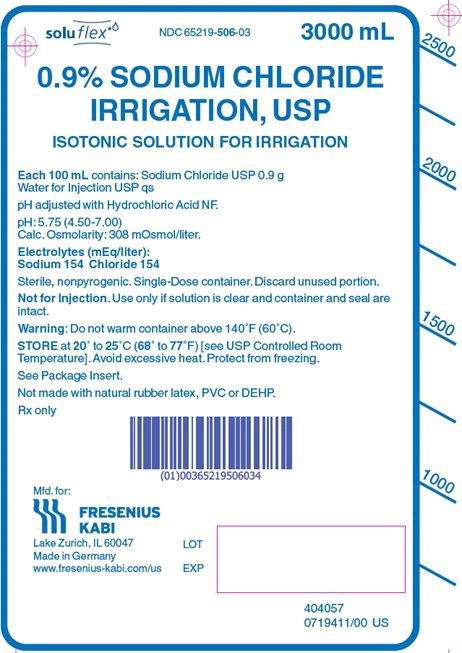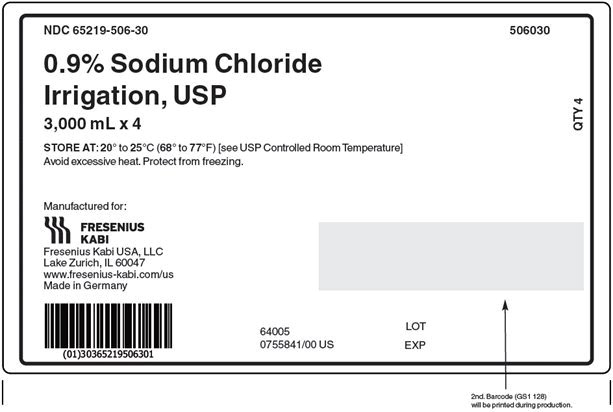 DRUG LABEL: Sodium chloride
NDC: 65219-502 | Form: INJECTION, SOLUTION
Manufacturer: Fresenius Kabi USA, LLC
Category: prescription | Type: HUMAN PRESCRIPTION DRUG LABEL
Date: 20251118

ACTIVE INGREDIENTS: SODIUM CHLORIDE 0.9 g/100 mL
INACTIVE INGREDIENTS: WATER; HYDROCHLORIC ACID

0.9% Sodium Chloride Irrigation, USP

Isotonic Solution for Irrigation.

For Irrigation Only.

Not for Injection.

Rx only

DESCRIPTION

Each 100 mL contains:

Sodium Chloride, USP 0.9 g; Water for Injection, USP qs pH adjusted with Hydrochloric Acid, NF

pH: 5.75 (4.50-7.00)

Calculated Osmolarity: 308 mOsmol/liter

Concentration of Electrolytes (mEq/liter): Sodium 154; Chloride 154

0.9% Sodium Chloride Irrigation, USP is sterile, nonpyrogenic, isotonic and contains no bacteriostatic or antimicrobial agents.

The formula of the active ingredient is:

Ingredient | Molecular Formula | Molecular Weight
Sodium Chloride, USP | NaCl | 58.44

The flexible plastic container is made from a multilayered film specifically developed for parenteral drugs. It contains no plasticizers. The solution contact layer is a copolymer of ethylene and propylene. The container is nontoxic and biologically inert.

The container-solution unit is a closed system and is not dependent upon entry of external air during administration.

Not made with natural rubber latex, PVC or DEHP.

CLINICAL PHARMACOLOGY

0.9% Sodium Chloride Irrigation is utilized for a variety of clinical indications such as sterile irrigation of body cavities, tissues or wounds, indwelling urethral catheters, surgical drainage tubes, and for washing, rinsing or soaking surgical dressings, instruments and laboratory specimens. It also serves as a diluent or vehicle for drugs used for irrigation or other pharmaceutical preparations.

0.9% Sodium Chloride Irrigation provides an isotonic saline irrigation identical in composition with 0.9% Sodium Chloride Injection (normal saline).

Physiological irrigation solutions are considered generally compatible with living tissues and organs.

Sodium, the major cation of the extracellular fluid, functions primarily in the control of water distribution, fluid balance, and osmotic pressure of body fluids. Sodium is also associated with chloride and bicarbonate in the regulation of the acid-base equilibrium of body fluid.

Chloride, the major extracellular anion, closely follows the metabolism of sodium, and changes in the acid-base balance of the body are reflected by changes in the chloride concentration.

INDICATIONS AND USAGE

0.9% Sodium Chloride Irrigation is indicated for all general irrigation, washing, rinsing and dilution purposes which permit use of a sterile, nonpyrogenic electrolyte solution.

CONTRAINDICATIONS

0.9% Sodium Chloride Irrigation is not for injection by usual parenteral routes.

An electrolyte solution should not be used for irrigation during electrosurgical procedures.

WARNINGS

FOR IRRIGATION ONLY. NOT FOR INJECTION.

Irrigating fluids have been demonstrated to enter the systemic circulation in relatively large volumes; thus, irrigation solutions must be regarded as systemic drugs.

Absorption of large amounts can cause fluid and/or solute overload resulting in dilution of serum electrolyte concentrations, overhydration, congested states or pulmonary edema.

The risk of dilutional states is inversely proportional to the electrolyte concentrations of the administered parenteral solutions. The risk of solute overload causing congested states with peripheral and pulmonary edema is directly proportional to the electrolyte concentration.

Do not warm container above 140°F (60°C).

After opening container, its contents should be used promptly to minimize the possibility of bacterial growth or pyrogen formation.

Discard unused portion of irrigating solution since it contains no preservatives.

PRECAUTIONS

General

Use aseptic technique when preparing and administering sterile irrigation solutions. Use only if solution is clear and container and seal are intact.

Do not use for irrigation that may result in absorption of large amounts of fluid into the blood.

Caution should be observed when the solution is used for continuous irrigation or allowed to “dwell” inside body cavities because of possible absorption into the blood stream and the production of circulatory overload.

When used for irrigation via appropriate irrigation equipment, the administration set should be attached promptly. Unused portions should be discarded and a fresh container of appropriate size used for the start up of each cycle or repeat procedure. For repeated irrigations of urethral catheters, a separate container should be used for each patient.

Laboratory Tests

Clinical evaluation and periodic laboratory determinations are necessary to monitor changes in fluid balance, electrolyte concentrations, and acid-base balance after prolonged irrigation, when fluid absorption is suspected, or whenever the condition of the patient warrants such evaluation.

Drug Interactions

Some additives may be incompatible. Consult with pharmacist. When introducing additives, use aseptic technique. Mix thoroughly. Do not store.

Carcinogenesis, Mutagenesis, Impairment of Fertility

Studies with 0.9% Sodium Chloride Irrigation have not been performed to evaluate carcinogenic potential, mutagenic potential, or effects on fertility.

Pregnancy

Teratogenic Effects

Animal reproduction studies have not been conducted with 0.9% Sodium Chloride Irrigation. It is also not known whether 0.9% Sodium Chloride Irrigation can cause fetal harm when administered to a pregnant woman or can affect reproduction capacity. 0.9% Sodium Chloride Irrigation should be given to a pregnant woman only if clearly needed.

Labor and Delivery

Safety and effectiveness of 0.9% Sodium Chloride Irrigation during labor and delivery have not been established. Caution should be exercised, and the fluid balance, glucose and electrolyte concentrations, and acid-base balance, of both mother and fetus should be evaluated periodically or whenever warranted by the condition of the patient or fetus.

Nursing Mothers

It is not known whether this drug is excreted in human milk. Because many drugs are excreted in human milk, caution should be exercised when 0.9% Sodium Chloride Irrigation is administered to a nursing woman.

Pediatric Use

The safety and effectiveness of 0.9% Sodium Chloride Irrigation in pediatric patients have not been established. Its limited use in pediatric patients has been inadequate to fully define proper dosage and limitations for use.

Geriatric Use

Clinical studies of 0.9% Sodium Chloride Irrigation did not include a sufficient number of patients age 65 years and over to determine whether they respond differently from younger subjects. In general, dose selection for an elderly patient should be cautious, usually starting at the low end of the dosing range, reflecting the greater frequency of decreased hepatic, renal, or cardiac function, and of concomitant disease or other drug therapy.

This drug is known to be substantially excreted by the kidney, and the risk of toxic reactions to this drug may be greater in patients with impaired renal function. Because elderly patients are more likely to have decreased renal function, care should be taken in dose selection, and it may be useful to monitor renal function. Frequent laboratory determinations and clinical evaluations are recommended to monitor changes in blood glucose, electrolyte concentrations, and renal function.

ADVERSE REACTIONS

Possible adverse effects arising from the irrigation of body cavities, tissues, or indwelling catheters and tubes can be minimized when proper procedures are followed. Displaced catheters or drainage tubes can lead to irrigation or infiltration of unintended structures or cavities. Excessive volume or pressure during irrigation of closed cavities may cause undue distension or disruption of tissues. Accidental contamination from careless technique may transmit infection.

If an adverse reaction does occur, discontinue administration of the irrigant, evaluate the patient, institute appropriate therapeutic countermeasures, and save the remainder of the fluid for examination if deemed necessary.

To report SUSPECTED ADVERSE REACTIONS, contact Fresenius Kabi USA, LLC at 1-800-551-7176 or FDA at 1-800-FDA-1088 or www.fda.gov/medwatch.

OVERDOSAGE

In the event of overhydration or solute overload, reevaluate the patient's condition, and institute appropriate corrective treatment. Intravascular volume overload may respond to hemodialysis. See WARNINGS, PRECAUTIONS, and ADVERSE REACTIONS.

DOSAGE AND ADMINISTRATION

As required for irrigation.

When used as a diluent, or vehicle for other drugs, the drug manufacturer's recommendations should be followed.

Some additives may be incompatible. Consult with pharmacist. When introducing additives, use aseptic techniques. Mix thoroughly. Do not store.

Solutions should be inspected visually for particulate matter and discoloration prior to administration, whenever solution and container permits.

HOW SUPPLIED

0.9% Sodium Chloride Irrigation, USP is supplied sterile and nonpyrogenic in single-dose flexible plastic containers.

Product Code | Unit of Sale | Each
502010 | NDC 65219-502-10 Package of 6 bags | NDC 65219-502-01 1000 mL fill in a 1500 mL bag
504020 | NDC 65219-504-20 Package of 5 bags | NDC 65219-504-02 2000 mL fill in a 2000 mL bag
506030 | NDC 65219-506-30 Package of 4 bags | NDC 65219-506-03 3000 mL fill in a 3000 mL bag

Exposure of pharmaceutical products to heat should be minimized. Avoid excessive heat. Protect from freezing. Store at 20° to 25°C (68° to 77°F) [see USP Controlled Room Temperature]; however, brief exposure up to 40°C (104°F) does not adversely affect the product.

Do not warm container above 140°F (60°C).

INSTRUCTIONS FOR USE:

Not for Injection. Not for use with pressurized irrigation systems.

Check solution container composition, lot number, and expiry date.

Irrigation solutions should be inspected visually for particulate matter and discoloration prior to administration, whenever solution and container permit.

Do not use if the solution is cloudy or precipitate is present.

Check the solution container for leaks by squeezing firmly. If leaks are found, discard.

The intact port cap provides visual tamper evidence. Do not use if port cap is prematurely removed. Maintain strict aseptic technique during handling.

To Add Medication:

1. Identify WHITE Additive Port with arrow pointing toward solution container.
2. Immediately before injecting additives, break off WHITE Additive Port Cap with the arrow pointing toward solution container.
3. Hold base of WHITE Additive Port.
4. Insert needle (18 – 23 gauge) through the center of the WHITE Additive Port's resealable septum and inject additives.
5. Mix solution container contents thoroughly.
6. WHITE additive port must be swabbed with disinfection agent before repuncturing.
7. Check admixture visually for particulate matter.

Preparation for Administration

1. Immediately before inserting the irrigation set, break off BLUE Administration Port Cap with the arrow pointing away from the solution container.
2. Use non-vented irrigation set or close the air-inlet on a vented set. Refer to directions for use accompanying the irrigation set.
3. Hold the base of the BLUE Administration Port, twist and push spike until fully inserted.
4. The BLUE Administration Port contains a self-sealing septum that helps prevent leakage after removing the spike. The Administration Port is not intended to be spiked more than once.
5. Suspend solution container from hanger hole.
6. For Single Use Only. Discard unused portion.

Manufactured for:

Lake Zurich, IL 60047

Made in Germany
www.fresenius-kabi.com/us

451818A
Revised: January 2025

PACKAGE LABEL – PRINCIPAL DISPLAY – 0.9% Sodium Chloride Irrigation, USP 1000 mL Bag Label

soluflex® NDC 65219-502-01 1000 mL

0.9% SODIUM CHLORIDE
IRRIGATION, USP

ISOTONIC SOLUTION FOR IRRIGATION

PACKAGE LABEL – PRINCIPAL DISPLAY – 0.9% Sodium Chloride Irrigation, USP 1000 mL Case Label

NDC 65219-502-10 502010

0.9% Sodium Chloride
Irrigation, USP

1,000 mL x 6

STORE AT: 20° to 25°C (68° to 77°F) [see USP Controlled Room Temperature]
Avoid excessive heat. Protect from freezing.

PACKAGE LABEL – PRINCIPAL DISPLAY – 0.9% Sodium Chloride Irrigation, USP 2000 mL Bag Label

soluflex® NDC 65219-504-02 2000 mL

0.9% SODIUM CHLORIDE
IRRIGATION, USP

ISOTONIC SOLUTION FOR IRRIGATION

PACKAGE LABEL – PRINCIPAL DISPLAY – 0.9% Sodium Chloride Irrigation, USP 2000 mL Case Label

NDC 65219-504-20 504020

0.9% Sodium Chloride
Irrigation, USP

2,000 mL x 5

STORE AT: 20° to 25°C (68° to 77°F) [see USP Controlled Room Temperature]
Avoid excessive heat. Protect from freezing.

PACKAGE LABEL – PRINCIPAL DISPLAY – 0.9% Sodium Chloride Irrigation, USP 3000 mL Bag Label

soluflex® NDC 65219-506-03 3000 mL

0.9% SODIUM CHLORIDE
IRRIGATION, USP

ISOTONIC SOLUTION FOR IRRIGATION

PACKAGE LABEL – PRINCIPAL DISPLAY – 0.9% Sodium Chloride Irrigation, USP 3000 mL Case Label

NDC 65219-506-30 506030

0.9% Sodium Chloride
Irrigation, USP

3,000 mL x 4

STORE AT: 20° to 25°C (68° to 77°F) [see USP Controlled Room Temperature]
Avoid excessive heat. Protect from freezing.